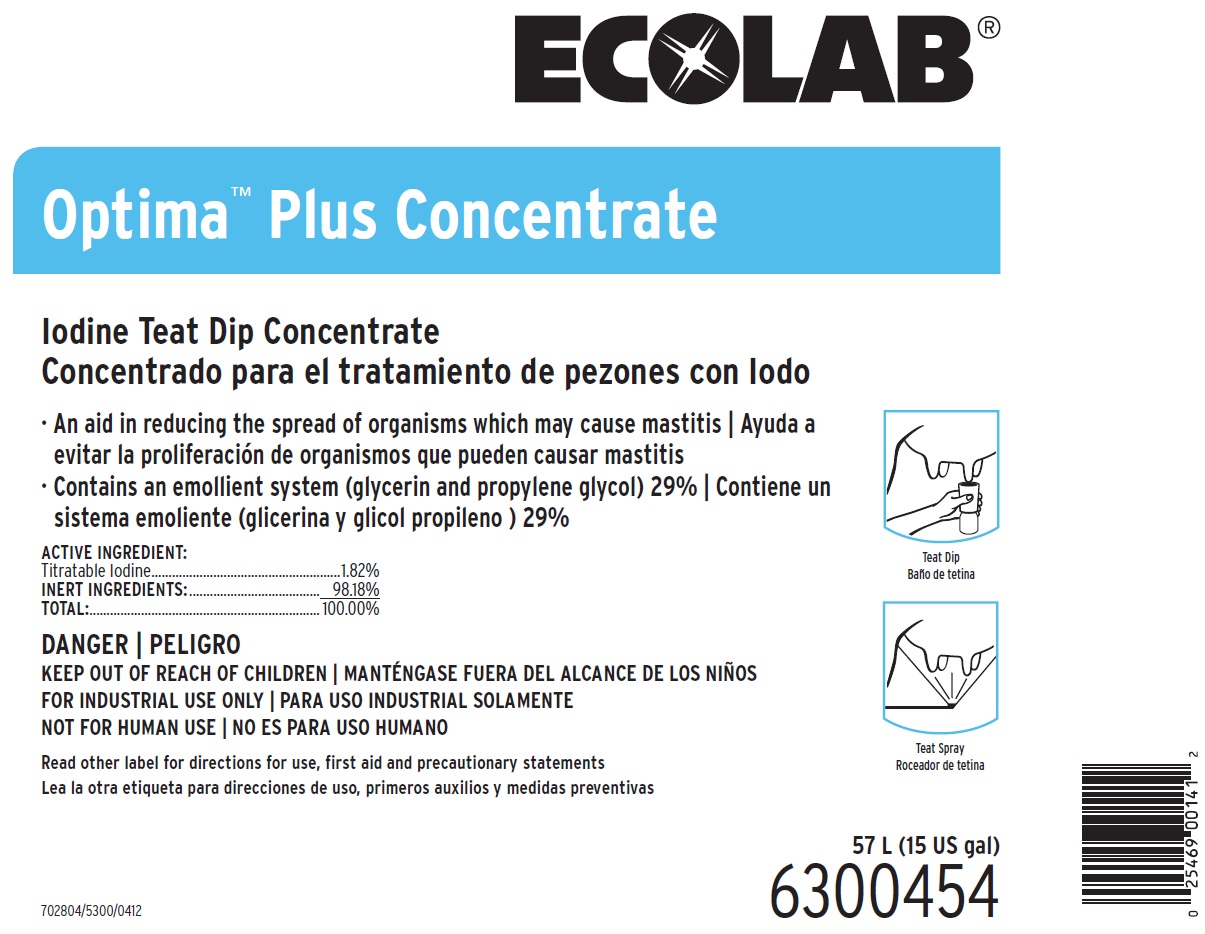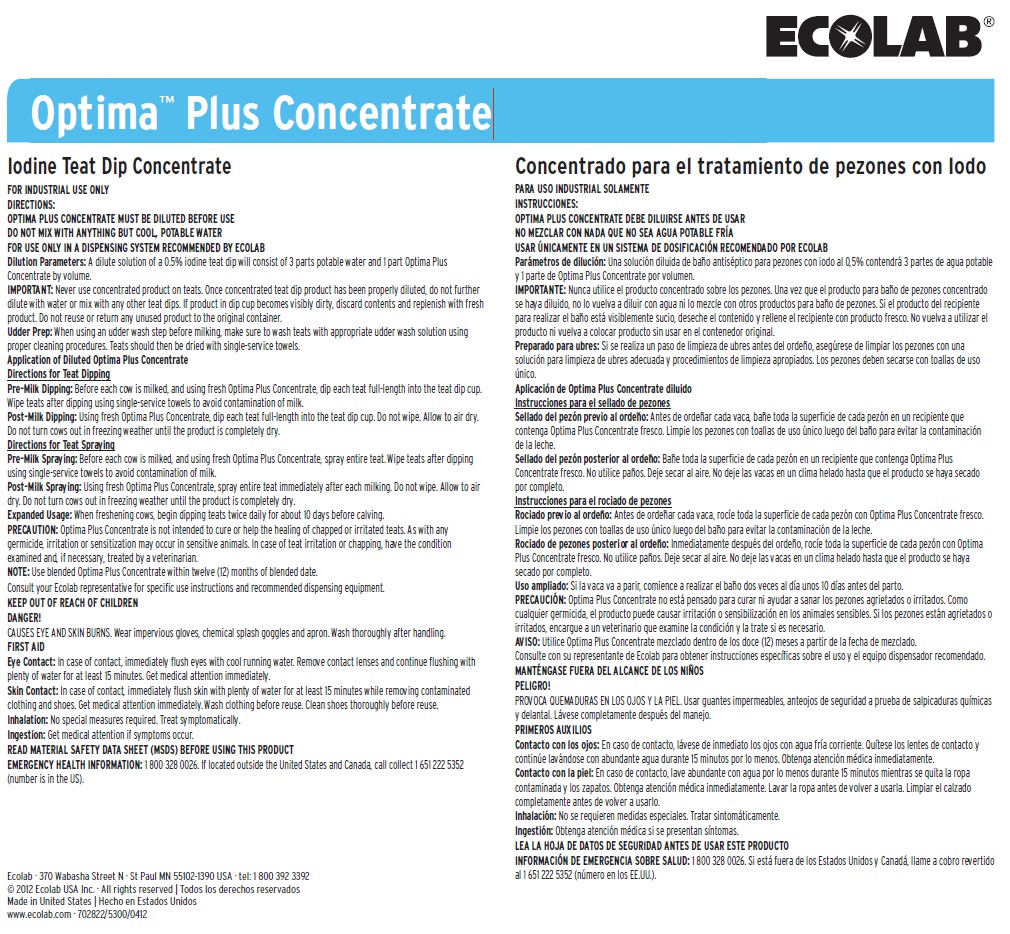 DRUG LABEL: Optima Plus Concentrate
NDC: 47593-141 | Form: SOLUTION
Manufacturer: Ecolab Inc.
Category: animal | Type: OTC ANIMAL DRUG LABEL
Date: 20251012

ACTIVE INGREDIENTS: IODINE 18.2 mg/1 mL
INACTIVE INGREDIENTS: WATER; GLYCERIN; PROPYLENE GLYCOL

SAFE HANDLING WARNING

DANGER

KEEP OUT OF REACH OF CHILDREN

FOR INDUSTRIAL USE ONLY

NOT FOR HUMAN USE

CAUSES EYE AND SKIN BURNS. Wear impervious gloves, chemical splash goggles and apron. Wash thoroughly after handling.

DIRECTIONS:

OPTIMA PLUS CONCENTRATE MUST BE DILUTED BEFORE USE

DO NOT MIX WITH ANYTHING BUT COOL, POTABLE WATER

FOR USE ONLY IN A DISPENSING SYSTEM RECOMMENDED BY ECOLAB

Dilution Parameters: A dilute solution of a 0.5% iodine teat dip will consist of 3 parts potable water and 1 part Optima Plus Concentrate by volume.

IMPORTANT: Never use concentrated product on teats. Once concentrated teat dip product has been properly diluted, do not further dilute with water or mix with any other teat dips. If product in dip cup becomes visibly dirty, discard contents and replenish with fresh product. Do not reuse or return any unused product to the original container.

Udder Prep: When using an udder wash step before milking, make sure to wash teats with appropriate udder wash solution using proper cleaning procedures. Teats should then be dried with single-service towels.

Application of Diluted Optima Plus Concentrate

Directions for Teat Dipping

Pre-Milk Dipping: Before each cow is milked, and using fresh Optima Plus Concentrate, dip each teat full-length into the teat dip cup. Wipe teats after dipping using single-service towels to avoid contamination of milk.

Post-Milk Dipping: Using fresh Optima Plus Concentrate, dip each teat full-length into the teat dip cup. Do not wipe. Allow to air dry. Do not turn cows out in freezing weather until the product is completely dry.

Directions for Teat Spraying

Pre-Milk Spraying: Before each cow is milked, and using fresh Optima Plus Concentrate, spray entire teat. Wipe teats after dipping using single-service towels to avoid contamination of milk.

Post-Milk Spraying: Using fresh Optima Plus Concentrate, spray entire teat immediately after each milking. Do not wipe. Allow to air dry. Do not turn cows out in freezing weather until the product is completely dry.

Expanded Usage: When freshening cows, begin dipping teats twice daily for about 10 days before calving.

PRECAUTION: Optima Plus Concentrate is not intended to cure or help the healing of chapped or irritated teats. As with any germicide, irritation or sensitization may occur in sensitive animals. In case of teat irritation or chapping, have the condition examined and, if necessary, treated by a veterinarian.

NOTE: Use blended Optima Plus Concentrate within twelve (12) months of blended date.

Consult your Ecolab representative for specific use instructions and recommended dispensing equipment.

OTHER SAFETY INFORMATION

FIRST AID

Eye Contact: In case of contact, immediately flush eyes with cool running water. Remove contact lenses and continue flushing with plenty of water for at least 15 minutes. Get medical attention immediately.

Skin Contact: In case of contact, immediately flush skin with plenty of water for at least 15 minutes while removing contaminated clothing and shoes. Get medical attention immediately. Wash clothing before reuse. Clean shoes thoroughly before reuse. Inhalation: No special measures required. Treat symptomatically.

Ingestion: Get medical attention if symptoms occur.

READ MATERIAL SAFETY DATA SHEET (MSDS) BEFORE USING THIS PRODUCT

EMERGENCY HEALTH INFORMATION: 1 800 328 0026. If located outside the United States and Canada, call collect 1 651 222 5352 (number is in the US).

Representative Label and Principal Display Panel

ECOLAB

Optima Plus Concentrate

Iodine Teat Dip Concentreate

An aidin reducing the spread of organisms which may cause mastitis

Contains an emollient system (glycerin and propylene glycol) 29%

ACTIVE INGREDIENT:

Titratable Iodine...............1.82%

INERT INGREDIENTS:...........98.18%

TOTAL:...............................100.00%

57l (15 US gal)

6300454

702804/5300/0412

Ecolab · 370 Wabasha Street N · St Paul MN 55102-1390 USA · tel: 1 800 392 3392

© 2012 Ecolab USA Inc. · All rights reserved

Made in United States

www.ecolab.com · 702822/5300/0412